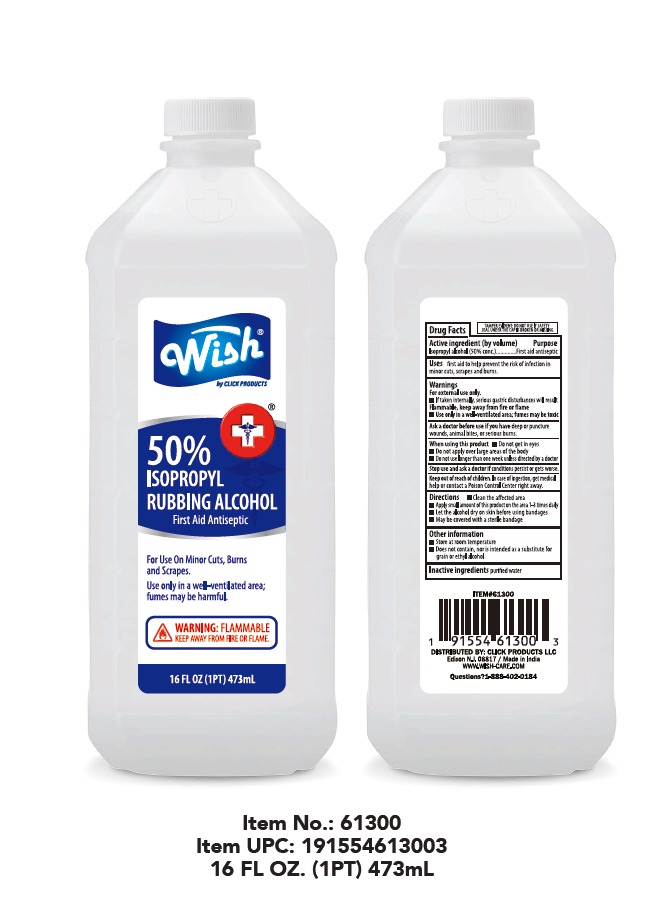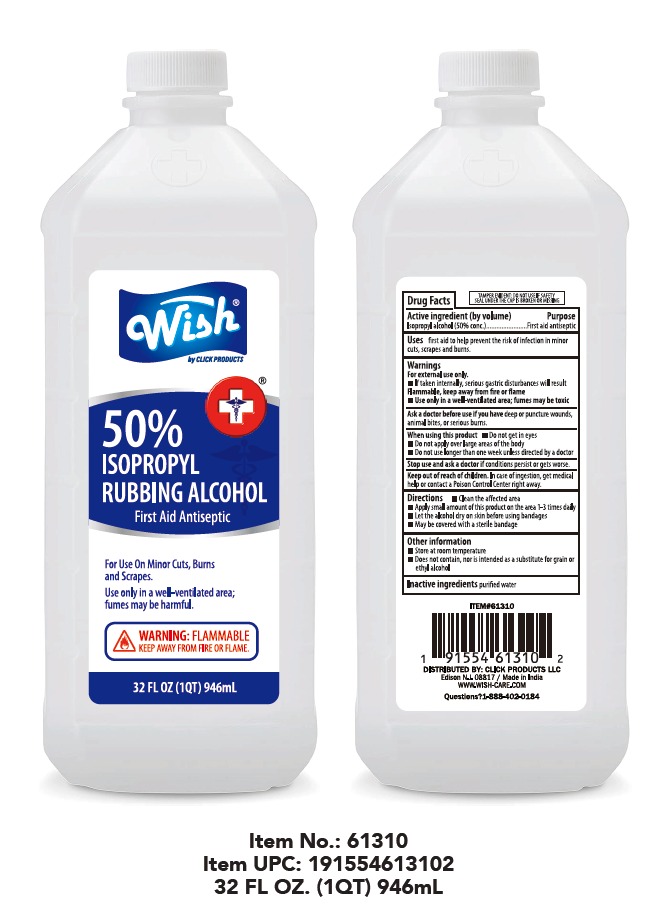 DRUG LABEL: WISH RUBBING ALCOHOL 50%
NDC: 84809-009 | Form: LIQUID
Manufacturer: LJ Pharma
Category: otc | Type: HUMAN OTC DRUG LABEL
Date: 20260129

ACTIVE INGREDIENTS: ISOPROPYL ALCOHOL 50 mL/100 mL
INACTIVE INGREDIENTS: WATER

Active Ingredient

Isopropyl Alcohol 50%

Purpose

FIRST AID ANTISEPTIC

Uses

First aid to help prevent the risk of infection in minor cuts, Scrapes & Burns.

Warnings

- For external use only
- IF taken internally, Serious gastric disturbances will result. Flammable,Keep away from fire or flame, heat, spark, electrical
- Use only in a well-ventilated area:Fumes may be toxic.

Ask a doctor before use if you havedeep or puncture wounds, Animal bites or serious burns.

When using this product:

- Do not get in the eyes
- Do not inhale
- Do not apply over large areas of the body
- Do not use longer than one week unless directed by doctor

Stop use and ask doctor ifconditions persist or get worse

Keep out of reach of children In case of ingestion, get medical help or contact a Poison Control Center right away.

Caution- Fumes can be acutely irritating to skin, eyes and the respiratory system. Do not apply to irritated skin or if excessive irritation develops. Avoid getting into the eyes or on mucous membranes. Avoid inhaling this product.

Directions

- Clean the affected Area
- Apply Small amount of this product on the area 1-3 times daily
- Let the alcohol dry on skin before using bandages.
- May be covered with a sterile bandag.
- If bandaged, let dry first

Other information

Store ate room temperature
Does not contain, nor is intended as a substitute for grain or ethyl alchol.

Inactive Ingredients

Purified Water